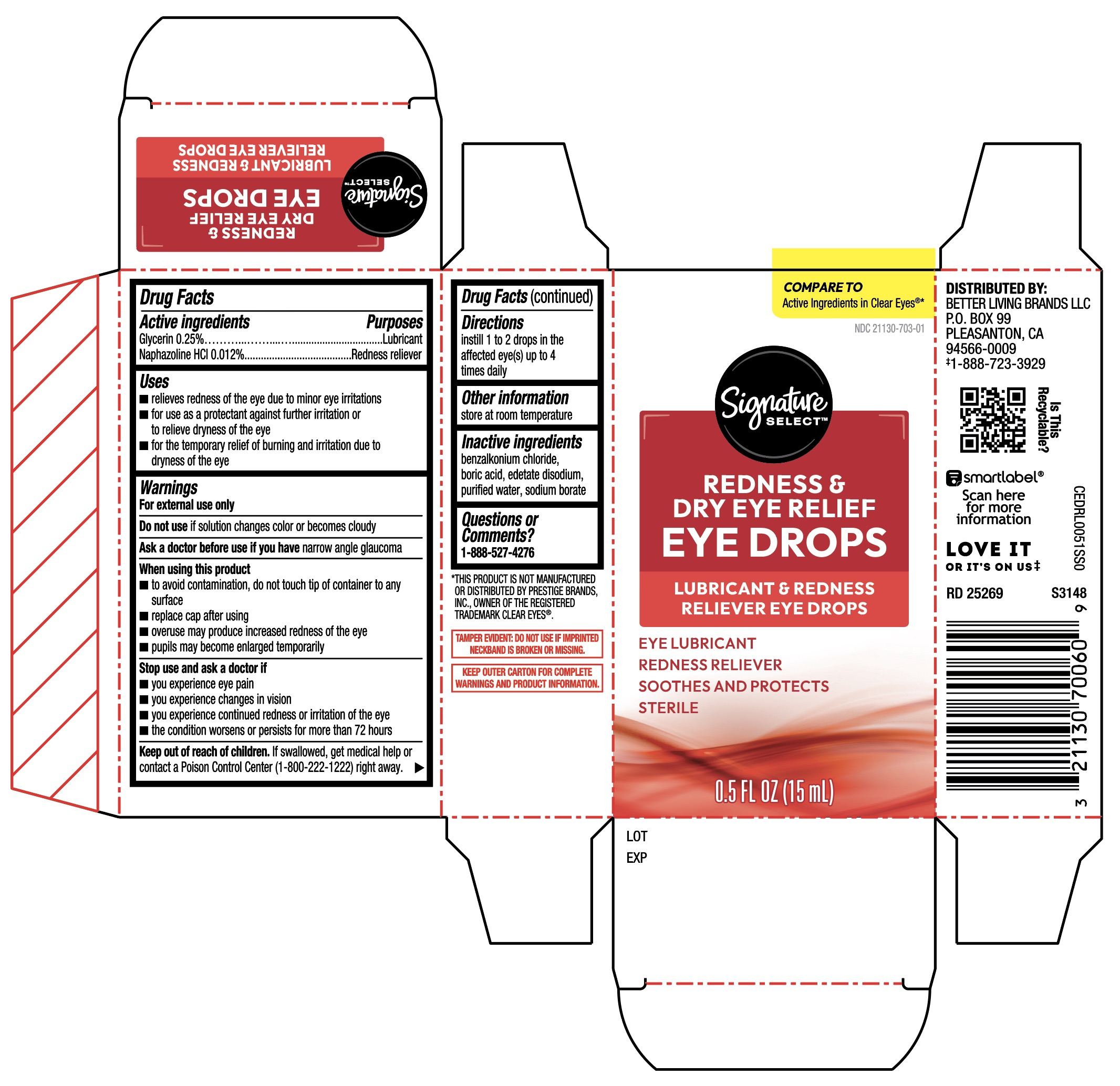 DRUG LABEL: Signature Care Eye Drops Redness and Dry Eye Relief
NDC: 21130-703 | Form: SOLUTION/ DROPS
Manufacturer: Better Living Brands LLC
Category: otc | Type: HUMAN OTC DRUG LABEL
Date: 20251219

ACTIVE INGREDIENTS: GLYCERIN 0.25 g/100 mL; NAPHAZOLINE HYDROCHLORIDE 0.012 g/100 mL
INACTIVE INGREDIENTS: BENZALKONIUM CHLORIDE; BORIC ACID; EDETATE DISODIUM; WATER; SODIUM BORATE

Signature Select Eye Drops Redness and Dry Eye Relief 15 mL (PLD)

Active ingredients

Glycerin 0.25%

Naphazoline hydrochloride 0.012%

Purposes

Glycerin Lubricant

Naphazoline hydrochloride Redness reliever

Uses

- for the relief of redness of the eye due to minor eye irritations
- for the temporary relief of burining and irritation due to dryness of the eye
- for use as a protectant against further irritation or dryness of the eye

Warnings

For external use only

Do not use

- if solution changes color or becomes cloudy

Ask a doctor before use if you have

narrow angle glaucoma

When using this product

- to avoid contamination, do not touch tip of container to any surface
- replace cap after using
- overuse may produce increased redness of the eye
- pupils may become enlarged temporarily

Stop use and ask a doctor if

- you experience eye pain
- changes in vision occur
- redness or irritation of the eye lasts
- condition worsens
- symptoms last for more than 72 hours

Keep out of reach of children

If swallowed, get medical help or contact a Poison Control Center (1-800-222-1222) right away.

Directions

Instill 1 or 2 drops in the affected eye(s) up to 4 times daily

Other information

- store at room temperature
- remove contact lenses before using

Inactive ingredients

benzalkonium chloride, boric acid, edetate disodium, purified water, sodium borate

Questions or Comments?

1-888-527-4276